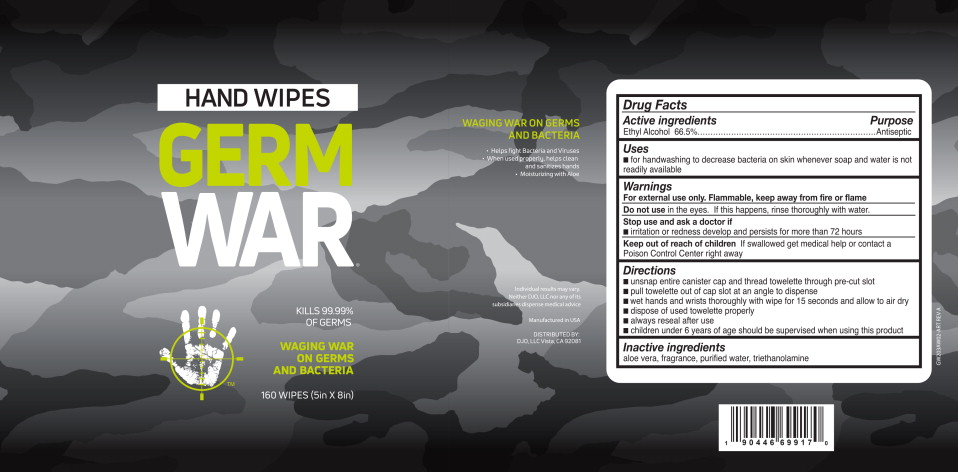 DRUG LABEL: Antiseptic Wipe
NDC: 80950-3111 | Form: CLOTH
Manufacturer: DJO LLC
Category: otc | Type: HUMAN OTC DRUG LABEL
Date: 20201214

ACTIVE INGREDIENTS: alcohol 665 mL/100 L
INACTIVE INGREDIENTS: aloe; water; trolamine

Drug Facts

Active ingredients

Ethyl Alcohol 66.5%

Purpose

Antiseptic

Uses

- for handwashing to decrease bacteria on skin whenever soap and water is not readily available
- helps prevent the risk of cross-contamination of bacteria that potentially can cause disease or infection

Warnings

For external use only. Flammable, keep away from fire or flame

Do not use in the eyes. If this happens, rinse thoroughly with water

Stop use and ask a doctor if

- irritation or redness develop and persists for more than 72 hours

Keep out of reach of children If swallowed get medical help or contact a Poison Control Center right away

Directions

- unsnap entire canister cap and thread towelette through pre-cut slot
- pull towelette out of cap slot at an angle to dispense
- wet hands and wrists thoroughly with wipe for 15 seconds and allow to air dry
- dispose of used towelette properly
- always reseal after use
- children under 6 years of age should be supervised when using this product

Inactive ingredients

aloe vera, fragrance, purified water, triethanolamine

Principal Display Panel - 160 Wipes Canister Label

HAND WIPES

GERM
WAR®

KILLS 99.99%
OF GERMS

WAGING WAR
ON GERMS
AND BACTERIA

160 WIPES (5IN X 8IN)